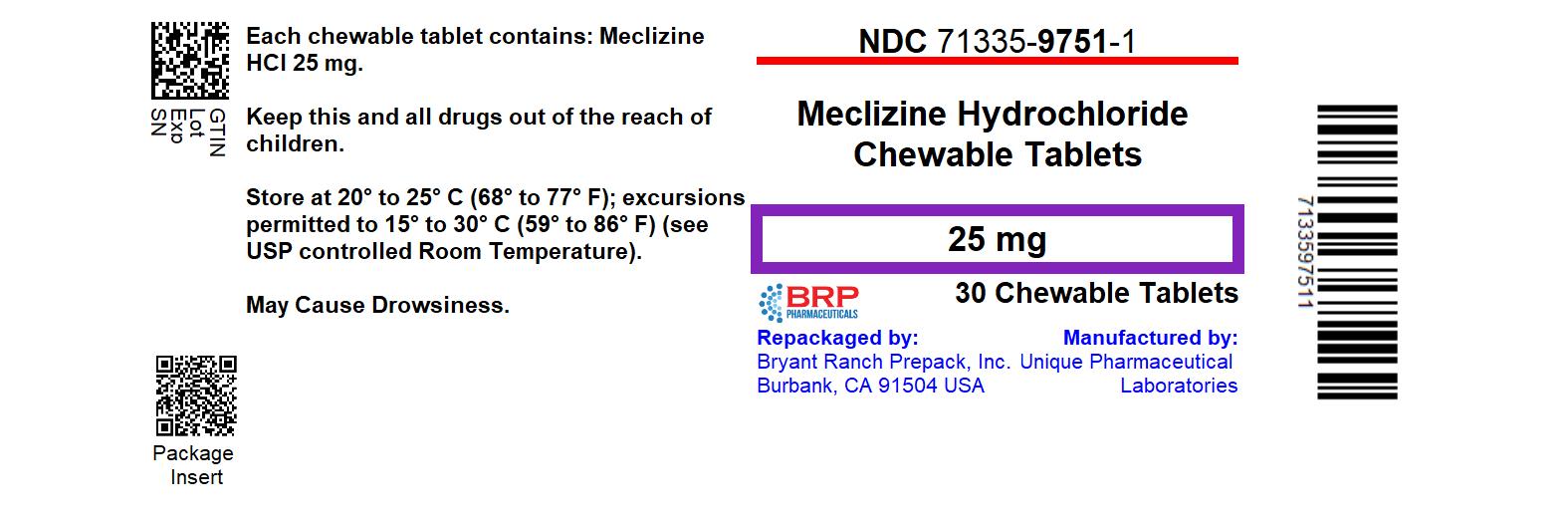 DRUG LABEL: Meclizine HCl
NDC: 71335-9751 | Form: TABLET, CHEWABLE
Manufacturer: Bryant Ranch Prepack
Category: otc | Type: HUMAN OTC DRUG LABEL
Date: 20241212

ACTIVE INGREDIENTS: MECLIZINE HYDROCHLORIDE 25 mg/1 1
INACTIVE INGREDIENTS: ASPARTAME; CROSCARMELLOSE SODIUM; DEXTROSE, UNSPECIFIED FORM; FD&C RED NO. 40; MAGNESIUM STEARATE; MALTODEXTRIN; MICROCRYSTALLINE CELLULOSE; RASPBERRY; SILICON DIOXIDE; SODIUM SULFATE ANHYDROUS; SUCROSE; TRIBASIC CALCIUM PHOSPHATE

Meclizine Hydrochloride Chewable Tablets 25 mg

Drug Facts Active ingredient (in each chewable tablet)

Meclizine HCl, USP 25 mg

Purpose

Antiemetic

Uses

prevents and treats nausea, vomiting or dizziness due to motion sickness.

Warnings

Do not use in children under 12 years of age unless directed by a doctor

Ask a doctor before use if you have

- glaucoma
- a breathing problem such as emphysema or chronic bronchitis
- trouble urinating due to an enlarged prostate gland

Ask a doctor or pharmacist before use if you are taking sedatives or tranquilizers.

When using this product

- may cause drowsiness
- alcohol, sedatives, and tranquilizers may increase drowsiness
- avoid alcoholic drinks
- use caution when driving a motor vehicle or operating machinery

PREGNANCY OR BREAST FEEDING

If pregnant or breast-feeding, ask a health professional before use.

Keep out of reach of children.

In case of overdose, get medical help or contact the Poison Control Center immediately.

Directions

- Dosage should be taken one hour before travel starts
- Adults and children 12 years and older: Chew 1-2 tablets once daily, or as directed by a doctor
- Children under 12 years: do not give this product to children under 12 years of age unless directed by a doctor

Other Information

- Phenylketonurics: Contains Phenylalanine 0.0025 mg per tablet
- Store at room temperature in a dry place
- Keep lid tightly closed

Inactive ingredients

aspartame, colloidal silicon dioxide, croscarmellose sodium, dextrose, lake of FD & C Red 40, magnesium stearate, maltodextrin, microcrystalline cellulose, raspberry flavor, sodium sulfate anhydrous, sucrose, tribasic calcium phosphate

Questions or comments?

Call 1-844-474-7464 Monday to Friday 8 AM - 5 PM ET

HOW SUPPLIED

NDC: 71335-9751-1: 30 Tablets in a BOTTLE

NDC: 71335-9751-2: 20 Tablets in a BOTTLE

NDC: 71335-9751-3: 25 Tablets in a BOTTLE

NDC: 71335-9751-4: 40 Tablets in a BOTTLE

NDC: 71335-9751-5: 60 Tablets in a BOTTLE

NDC: 71335-9751-6: 90 Tablets in a BOTTLE

NDC: 71335-9751-7: 8 Tablets in a BOTTLE

NDC: 71335-9751-8: 14 Tablets in a BOTTLE

NDC: 71335-9751-9: 10 Tablets in a BOTTLE

NDC: 71335-9751-0: 120 Tablets in a BOTTLE

PACKAGE LABEL

Meclizine 25 mg Chewable